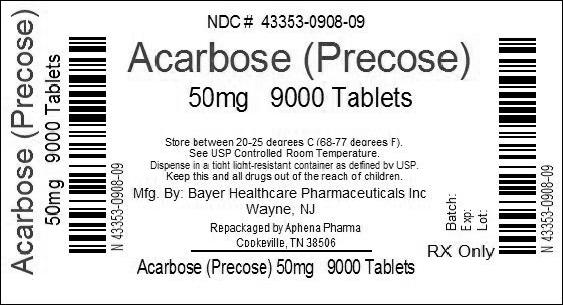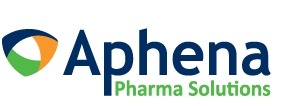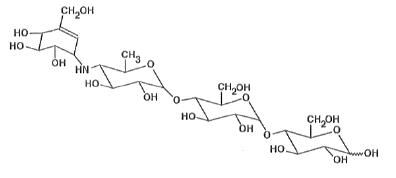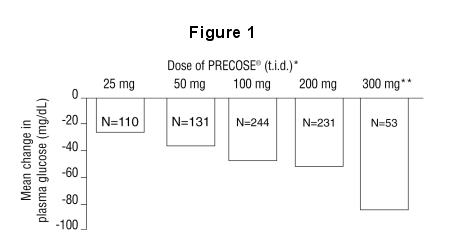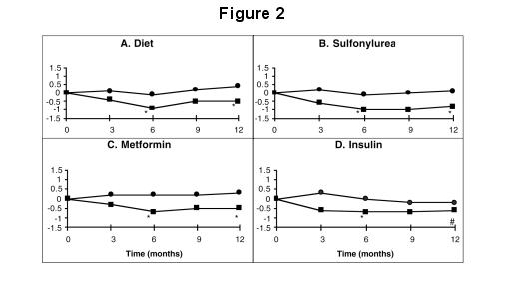 DRUG LABEL: Precose
NDC: 43353-908 | Form: TABLET
Manufacturer: Aphena Pharma Solutions - Tennessee, LLC
Category: prescription | Type: HUMAN PRESCRIPTION DRUG LABEL
Date: 20140529

ACTIVE INGREDIENTS: ACARBOSE 50 mg/1 1
INACTIVE INGREDIENTS: STARCH, CORN; CELLULOSE, MICROCRYSTALLINE; MAGNESIUM STEARATE; SILICON DIOXIDE

PRECOSE
(acarbose tablets)

DESCRIPTION

PRECOSE® (acarbose tablets) is an oral alpha-glucosidase inhibitor for use in the management of type 2 diabetes mellitus. Acarbose is an oligosaccharide which is obtained from fermentation processes of a microorganism, Actinoplanes utahensis, and is chemically known as O-4,6-dideoxy- 4-[[(1S,4R,5S,6S)-4,5,6-trihydroxy-3-(hydroxymethyl)-2-cyclohexen-1-yl]amino]-α-D-glucopyranosyl-(1 → 4)-O-α-D-glucopyranosyl-(1 → 4)-D-glucose. It is a white to off-white powder with a molecular weight of 645.6. Acarbose is soluble in water and has a pKa of 5.1. Its empirical formula is C25H43NO18 and its chemical structure is as follows:

PRECOSE is available as 25 mg, 50 mg and 100 mg tablets for oral use. The inactive ingredients are starch, microcrystalline cellulose, magnesium stearate, and colloidal silicon dioxide.

CLINICAL PHARMACOLOGY

Acarbose is a complex oligosaccharide that delays the digestion of ingested carbohydrates,
thereby resulting in a smaller rise in blood glucose concentration following meals. As a consequence of plasma glucose reduction, PRECOSE reduces levels of glycosylated hemoglobin in patients with type 2 diabetes mellitus. Systemic non-enzymatic protein glycosylation, as reflected by levels of glycosylated hemoglobin, is a function of average blood glucose concentration over time.

Mechanism of Action:

In contrast to sulfonylureas, PRECOSE does not enhance insulin secretion. The antihyperglycemic action of acarbose results from a competitive, reversible inhibition of pancreatic alpha-amylase and membrane-bound intestinal alpha-glucoside hydrolase enzymes. Pancreatic alpha-amylase hydrolyzes complex starches to oligosaccharides in the lumen of the small intestine, while the membrane-bound intestinal alpha-glucosidases hydrolyze oligosaccharides, trisaccharides, and disaccharides to glucose and other monosaccharides in the brush border of the small intestine. In diabetic patients, this enzyme inhibition results in a delayed glucose absorption and a lowering of postprandial hyperglycemia.

Because its mechanism of action is different, the effect of PRECOSE to enhance glycemic control is additive to that of sulfonylureas, insulin or metformin when used in combination. In addition, PRECOSE diminishes the insulinotropic and weight-increasing effects of sulfonylureas.

Acarbose has no inhibitory activity against lactase and consequently would not be expected to induce lactose intolerance.

Pharmacokinetics:

Absorption

In a study of 6 healthy men, less than 2% of an oral dose of acarbose was absorbed as active drug, while approximately 35% of total radioactivity from a ^14C-labeled oral dose was absorbed. An average of 51% of an oral dose was excreted in the feces as unabsorbed drug-related radioactivity within 96 hours of ingestion. Because acarbose acts locally within the gastrointestinal tract, this low systemic bioavailability of parent compound is therapeutically desired. Following oral dosing of healthy volunteers with ^14C-labeled acarbose, peak plasma concentrations of radioactivity were attained 14–24 hours after dosing, while peak plasma concentrations of active drug were attained at approximately 1 hour. The delayed absorption of acarbose-related radioactivity reflects the absorption of metabolites that may be formed by either intestinal bacteria or intestinal enzymatic hydrolysis.

Metabolism

Acarbose is metabolized exclusively within the gastrointestinal tract, principally by intestinal bacteria, but also by digestive enzymes. A fraction of these metabolites (approximately 34% of the dose) was absorbed and subsequently excreted in the urine. At least 13 metabolites have been separated chromatographically from urine specimens. The major metabolites have been identified as 4-methylpyrogallol derivatives (that is, sulfate, methyl, and glucuronide conjugates). One metabolite (formed by cleavage of a glucose molecule from acarbose) also has alpha-glucosidase inhibitory activity. This metabolite, together with the parent compound, recovered from the urine, accounts for less than 2% of the total administered dose.

Excretion

The fraction of acarbose that is absorbed as intact drug is almost completely excreted by the kidneys. When acarbose was given intravenously, 89% of the dose was recovered in the urine as active drug within 48 hours. In contrast, less than 2% of an oral dose was recovered in the urine as active (that is, parent compound and active metabolite) drug. This is consistent with the low bioavailability of the parent drug. The plasma elimination half-life of acarbose activity is approximately 2 hours in healthy volunteers. Consequently, drug accumulation does not occur with three times a day (t.i.d.) oral dosing.

Special Populations

The mean steady-state area under the curve (AUC) and maximum concentrations of acarbose were approximately 1.5 times higher in elderly compared to young volunteers; however, these differences were not statistically significant. Patients with severe renal impairment (Clcr < 25 mL/min/1.73m^2) attained about 5 times higher peak plasma concentrations of acarbose and 6 times larger AUCs than volunteers with normal renal function. No studies of acarbose pharmacokinetic parameters according to race have been performed. In U.S. controlled clinical studies of PRECOSE in patients with type 2 diabetes mellitus, reductions in glycosylated hemoglobin levels were similar in Caucasians (n=478) and African-Americans (n=167), with a trend toward a better response in Latinos (n=132).

Drug-Drug Interactions

Studies in healthy volunteers have shown that PRECOSE has no effect on either the pharmacokinetics or pharmacodynamics of nifedipine, propranolol, or ranitidine. PRECOSE did not interfere with the absorption or disposition of the sulfonylurea glyburide in diabetic patients. PRECOSE may affect digoxin bioavailability and may require dose adjustment of digoxin by 16% (90% confidence interval: 8-23%), decrease mean Cmaxof digoxin by 26% (90% confidence interval: 16–34%) and decreases mean trough concentrations of digoxin by 9% (90% confidence limit: 19% decrease to 2% increase). (See PRECAUTIONS, Drug Interactions.)

The amount of metformin absorbed while taking PRECOSE was bioequivalent to the amount absorbed when taking placebo, as indicated by the plasma AUC values. However, the peak plasma level of metformin was reduced by approximately 20% when taking PRECOSE due to a slight delay in the absorption of metformin. There is little if any clinically significant interaction between PRECOSE and metformin.

CLINICAL TRIALS

Clinical Experience from Dose Finding Studies in Type 2 Diabetes Mellitus Patients on Dietary Treatment Only: Results from six controlled, fixed-dose, monotherapy studies of PRECOSE in the treatment of type 2 diabetes mellitus, involving 769 PRECOSE-treated patients, were combined and a weighted average of the difference from placebo in the mean change from baseline in glycosylated hemoglobin (HbA1c) was calculated for each dose level as presented below:

Table 1 Mean Placebo-Subtracted Change in HbA1c in Fixed-Dose Monotherapy Studies
Dose of PRECOSE [PRECOSE was statistically significantly different from placebo at all doses. Although there were no statistically significant differences among the mean results for doses ranging from 50 to 300 mg t.i.d., some patients may derive benefit by increasing the dosage from 50 to 100 mg t.i.d.] | N | Change in HbA1c % | p-Value
25 mg t.i.d. | 110 | -0.44 | 0.0307
50 mg t.i.d. | 131 | -0.77 | 0.0001
100 mg t.i.d. | 244 | -0.74 | 0.0001
200 mg t.i.d. [Although studies utilized a maximum dose of 200 or 300 mg t.i.d., the maximum recommended dose for patients < 60 kg is 50 mg t.i.d.; the maximum recommended dose for patients > 60 kg is 100 mg t.i.d.] | 231 | -0.86 | 0.0001
300 mg t.i.d. | 53 | -1.00 | 0.0001

Results from these six fixed-dose, monotherapy studies were also combined to derive a weighted average of the difference from placebo in mean change from baseline for one-hour postprandial plasma glucose levels as shown in the following figure:

* PRECOSE was statistically significantly different from placebo at all doses with respect to effect on one-hour postprandial plasma glucose.

** The 300 mg t.i.d. PRECOSE regimen was superior to lower doses, but there were no statistically significant differences from 50 to 200 mg t.i.d.

Clinical Experience in Type 2 Diabetes Mellitus Patients on Monotherapy, or in Combination with Sulfonylureas, Metformin or Insulin: PRECOSE was studied as monotherapy and as combination therapy to sulfonylurea, metformin, or insulin treatment. The treatment effects on HbA1c levels and one-hour postprandial glucose levels are summarized for four placebo-controlled, double-blind, randomized studies conducted in the United States in Tables 2 and 3, respectively. The placebo-subtracted treatment differences, which are summarized below, were statistically significant for both variables in all of these studies.

Study 1 (n=109) involved patients on background treatment with diet only. The mean effect of the addition of PRECOSE to diet therapy was a change in HbA1c of -0.78%, and an improvement of one-hour postprandial glucose of -74.4 mg/dL.

In Study 2 (n=137), the mean effect of the addition of PRECOSE to maximum sulfonylurea therapy was a change in HbA1c of -0.54%, and an improvement of one-hour postprandial glucose of -33.5 mg/dL.

In Study 3 (n=147), the mean effect of the addition of PRECOSE to maximum metformin therapy was a change in HbA1c of -0.65%, and an improvement of one-hour postprandial glucose of -34.3 mg/dL.

Study 4 (n=145) demonstrated that PRECOSE added to patients on background treatment with insulin resulted in a mean change in HbA1c of -0.69%, and an improvement of one-hour postprandial glucose of -36.0 mg/dL.

A one year study of PRECOSE as monotherapy or in combination with sulfonylurea, metformin or insulin treatment was conducted in Canada in which 316 patients were included in the primary efficacy analysis (Figure 2). In the diet, sulfonylurea and metformin groups, the mean decrease in HbA1c produced by the addition of PRECOSE was statistically significant at six months, and this effect was persistent at one year. In the PRECOSE-treated patients on insulin, there was a statistically significant reduction in HbA1c at six months, and a trend for a reduction at one year.

Table 2: Effect of Precose on HbA1c
 |  | HbA1c (%) [HbA1c Normal Range: 4-6%]
Study | Treatment | Mean Baseline | Mean change from baseline [After four months treatment in Study 1, and six months in Studies 2, 3, and 4] | Treatment Difference | p-Value
1 | Placebo Plus Diet | 8.67 | +0.33 | — | —
1 | PRECOSE 100 mg t.i.d. Plus Diet | 8.69 | -0.45 | -0.78 | 0.0001
2 | Placebo Plus SFU [SFU, sulfonylurea, maximum dose] | 9.56 | +0.24 | — | —
2 | PRECOSE 50-300 [Although studies utilized a maximum dose of up to 300 mg t.i.d., the maximum recommended dose for patients = 60 kg is 50 mg t.i.d.; the maximum recommended dose for patients > 60 kg is 100 mg t.i.d] mg t.i.d. Plus SFU | 9.64 | -0.30 | -0.54 | 0.0096
3 | Placebo Plus Metformin [Metformin dosed at 2000 mg/day or 2500 mg/day] | 8.17 | +0.08 [Results are adjusted to a common baseline of 8.33%] | — | —
3 | PRECOSE 50-100 mg t.i.d. Plus Metformin | 8.46 | -0.57 g | -0.65 | 0.0001
4 | Placebo Plus Insulin [Mean dose of insulin 61 U/day] | 8.69 | +0.11 | — | —
4 | PRECOSE 50-100 mg t.i.d. Plus Insulin | 8.77 | -0.58 | -0.69 | 0.0001

 |  | One-Hour Postprandial Glucose (mg/dL)
Study | Treatment | Mean | Mean change | Treatment | p-Value
 |  | Baseline | from baseline [After four months treatment in Study 1, and six months in Studies 2, 3, and 4] | Difference
1 | Placebo Plus Diet | 297.1 | +31.8 | — | —
 | PRECOSE 100 mg t.i.d. | 299.1 | -42.6 | -74.4 | 0.0001
 | Plus Diet
2 | Placebo Plus SFU [SFU, sulfonylurea, maximum dose] | 308.6 | +6.2 | — | —
 | PRECOSE 50-300 [Although studies utilized a maximum dose of up to 300 mg t.i.d., the maximum recommended dose for patients ≤ 60 kg is 50 mg t.i.d.; the maximum recommended dose for patients > 60 kg is 100 mg t.i.d.] mg t.i.d. | 311.1 | -27.3 | -33.5 | 0.0017
 | Plus SFU
3 | Placebo Plus Metformin [Metformin dosed at 2000 mg/day or 2500 mg/day] | 263.9 | +3.3 [Results are adjusted to a common baseline of 273 mg/dL] | — | —
 | PRECOSE 50-100 mg t.i.d. | 283.0 | -31.0 | -34.3 | 0.0001
 | Plus Metformin
4 | Placebo Plus Insulin [Mean dose of insulin 61 U/day] | 279.2 | +8.0 | — | —
 | PRECOSE 50-100 mg t.i.d. | 277.8 | -28.0 | -36.0 | 0.0178
 | Plus Insulin

Figure 2: Effects of PRECOSE (■) and Placebo (●) on mean change in HbA1c levels from baseline throughout a one-year study in patients with type 2 diabetes mellitus when used in combination with: (A) diet alone; (B) sulfonylurea; (C) metformin; or (D) insulin. Treatment differences at 6 and 12 months were tested: * p < 0.01; # p = 0.077.

INDICATIONS AND USAGE

PRECOSE is indicated as an adjunct to diet and exercise to improve glycemic control in adults with type 2 diabetes mellitus.

CONTRAINDICATIONS

PRECOSE is contraindicated in patients with known hypersensitivity to the drug. Precose is contraindicated in patients with diabetic ketoacidosis or cirrhosis. PRECOSE is also contraindicated in patients with inflammatory bowel disease, colonic ulceration, partial intestinal obstruction or in patients predisposed to intestinal obstruction. In addition, PRECOSE is contraindicated in patients who have chronic intestinal diseases associated with marked disorders of digestion or absorption and in patients who have conditions that may deteriorate as a result of increased gas formation in the intestine.

PRECAUTIONS

General

Macrovascular Outcomes

There have been no clinical studies establishing conclusive evidence of macrovascular risk reduction with PRECOSE or any other anti-diabetic drug.

Hypoglycemia

Because of its mechanism of action, PRECOSE when administered alone should not cause hypoglycemia in the fasted or postprandial state. Sulfonylurea agents or insulin may cause hypoglycemia. Because PRECOSE given in combination with a sulfonylurea or insulin will cause a further lowering of blood glucose, it may increase the potential for hypoglycemia. Hypoglycemia does not occur in patients receiving metformin alone under usual circumstances of use, and no increased incidence of hypoglycemia was observed in patients when PRECOSE was added to metformin therapy. Oral glucose (dextrose), whose absorption is not inhibited by PRECOSE, should be used instead of sucrose (cane sugar) in the treatment of mild to moderate hypoglycemia. Sucrose, whose hydrolysis to glucose and fructose is inhibited by PRECOSE, is unsuitable for the rapid correction of hypoglycemia. Severe hypoglycemia may require the use of either intravenous glucose infusion or glucagon injection.

Elevated Serum Transaminase Levels

In long-term studies (up to 12 months, and including PRECOSE doses up to 300 mg t.i.d.) conducted in the United States, treatment-emergent elevations of serum transaminases (AST and/or ALT) above the upper limit of normal (ULN), greater than 1.8 times the ULN, and greater than 3 times the ULN occurred in 14%, 6%, and 3%, respectively, of PRECOSE-treated patients as compared to 7%, 2%, and 1%, respectively, of placebo-treated patients. Although these differences between treatments were statistically significant, these elevations were asymptomatic, reversible, more common in females, and, in general, were not associated with other evidence of liver dysfunction. In addition, these serum transaminase elevations appeared to be dose related. In US studies including PRECOSE doses up to the maximum approved dose of 100 mg t.i.d., treatment-emergent elevations of AST and/or ALT at any level of severity were similar between PRECOSE-treated patients and placebo-treated patients (p ≥ 0.496).

In approximately 3 million patient-years of international postmarketing experience with PRECOSE, 62 cases of serum transaminase elevations > 500 IU/L (29 of which were associated with jaundice) have been reported. Forty-one of these 62 patients received treatment with 100 mg t.i.d. or greater and 33 of 45 patients for whom weight was reported weighed < 60 kg. In the 59 cases where follow-up was recorded, hepatic abnormalities improved or resolved upon discontinuation of PRECOSE in 55 and were unchanged in two. Cases of fulminant hepatitis with fatal outcome have been reported; the relationship to acarbose is unclear.

Loss of Control of Blood Glucose

When diabetic patients are exposed to stress such as fever, trauma, infection, or surgery, a temporary loss of control of blood glucose may occur. At such times, temporary insulin therapy may be necessary.

Information for Patients

Patients should be told to take PRECOSE orally three times a day at the start (with the first bite) of each main meal. It is important that patients continue to adhere to dietary instructions, a regular exercise program, and regular testing of urine and/or blood glucose.

PRECOSE itself does not cause hypoglycemia even when administered to patients in the fasted state. Sulfonylurea drugs and insulin, however, can lower blood sugar levels enough to cause symptoms or sometimes life-threatening hypoglycemia. Because PRECOSE given in combination with a sulfonylurea or insulin will cause a further lowering of blood sugar, it may increase the hypoglycemic potential of these agents. Hypoglycemia does not occur in patients receiving metformin alone under usual circumstances of use, and no increased incidence of hypoglycemia was observed in patients when PRECOSE was added to metformin therapy. The risk of hypoglycemia, its symptoms and treatment, and conditions that predispose to its development should be well understood by patients and responsible family members. Because PRECOSE prevents the breakdown of table sugar, patients should have a readily available source of glucose (dextrose, D-glucose) to treat symptoms of low blood sugar when taking PRECOSE in combination with a sulfonylurea or insulin.

If side effects occur with PRECOSE, they usually develop during the first few weeks of therapy. They are most commonly mild-to-moderate gastrointestinal effects, such as flatulence, diarrhea, or abdominal discomfort, and generally diminish in frequency and intensity with time.

Laboratory Tests:

Therapeutic response to PRECOSE should be monitored by periodic blood glucose tests. Measurement of glycosylated hemoglobin levels is recommended for the monitoring of long-term glycemic control.

PRECOSE, particularly at doses in excess of 50 mg t.i.d., may give rise to elevations of serum transaminases and, in rare instances, hyperbilirubinemia. It is recommended that serum transaminase levels be checked every 3 months during the first year of treatment with PRECOSE and periodically thereafter. If elevated transaminases are observed, a reduction in dosage or withdrawal of therapy may be indicated, particularly if the elevations persist.

Renal Impairment:

Plasma concentrations of PRECOSE in renally impaired volunteers were proportionally increased relative to the degree of renal dysfunction. Long-term clinical trials in diabetic patients with significant renal dysfunction (serum creatinine > 2.0 mg/dL) have not been conducted. Therefore, treatment of these patients with PRECOSE is not recommended.

Drug Interactions

Certain drugs tend to produce hyperglycemia and may lead to loss of blood glucose control. These drugs include the thiazides and other diuretics, corticosteroids, phenothiazines, thyroid products, estrogens, oral contraceptives, phenytoin, nicotinic acid, sympathomimetics, calcium channel-blocking drugs, and isoniazid. When such drugs are administered to a patient receiving PRECOSE, the patient should be closely observed for loss of blood glucose control. When such drugs are withdrawn from patients receiving PRECOSE in combination with sulfonylureas or insulin, patients should be observed closely for any evidence of hypoglycemia.

Patients Receiving Sulfonylureas or Insulin: Sulfonylurea agents or insulin may cause hypoglycemia. PRECOSE given in combination with a sulfonylurea or insulin may cause a further lowering of blood glucose and may increase the potential for hypoglycemia. If hypoglycemia occurs, appropriate adjustments in the dosage of these agents should be made. Very rarely, individual cases of hypoglycemic shock have been reported in patients receiving PRECOSE therapy in combination with sulfonylureas and/or insulin.

Intestinal adsorbents (for example, charcoal) and digestive enzyme preparations containing carbohydrate-splitting enzymes (for example, amylase, pancreatin) may reduce the effect of PRECOSE and should not be taken concomitantly.

PRECOSE has been shown to change the bioavailability of digoxin when they are coadministered, which may require digoxin dose adjustment. (See CLINICAL PHARMACOLOGY, Drug-Drug Interactions .

Carcinogenesis, Mutagenesis, and Impairment of Fertility

Eight carcinogenicity studies were conducted with acarbose. Six studies were performed in rats (two strains, Sprague-Dawley and Wistar) and two studies were performed in hamsters.

In the first rat study, Sprague-Dawley rats received acarbose in feed at high doses (up to approximately 500 mg/kg body weight) for 104 weeks. Acarbose treatment resulted in a significant increase in the incidence of renal tumors (adenomas and adenocarcinomas) and benign Leydig cell tumors. This study was repeated with a similar outcome. Further studies were performed to separate direct carcinogenic effects of acarbose from indirect effects resulting from the carbohydrate malnutrition induced by the large doses of acarbose employed in the studies. In one study using Sprague-Dawley rats, acarbose was mixed with feed but carbohydrate deprivation was prevented by the addition of glucose to the diet. In a 26-month study of Sprague-Dawley rats, acarbose was administered by daily postprandial gavage so as to avoid the pharmacologic effects of the drug. In both of these studies, the increased incidence of renal tumors found in the original studies did not occur. Acarbose was also given in food and by postprandial gavage in two separate studies in Wistar rats. No increased incidence of renal tumors was found in either of these Wistar rat studies. In two feeding studies of hamsters, with and without glucose supplementation, there was also no evidence of carcinogenicity.

Acarbose did not induce any DNA damage in vitro in the CHO chromosomal aberration assay, bacterial mutagenesis (Ames) assay, or a DNA binding assay. In vivo, no DNA damage was detected in the dominant lethal test in male mice, or the mouse micronucleus test.

Fertility studies conducted in rats after oral administration produced no untoward effect on fertility or on the overall capability to reproduce.

Pregnancy

Teratogenic Effects: Pregnancy Category B

The safety of PRECOSE in pregnant women has not been established. Reproduction studies have been performed in rats at doses up to 480 mg/kg (corresponding to 9 times the exposure in humans, based on drug blood levels) and have revealed no evidence of impaired fertility or harm to the fetus due to acarbose. In rabbits, reduced maternal body weight gain, probably the result of the pharmacodynamic activity of high doses of acarbose in the intestines, may have been responsible for a slight increase in the number of embryonic losses. However, rabbits given 160 mg/kg acarbose (corresponding to 10 times the dose in man, based on body surface area) showed no evidence of embryotoxicity and there was no evidence of teratogenicity at a dose 32 times the dose in man (based on body surface area). There are, however, no adequate and well-controlled studies of PRECOSE in pregnant women. Because animal reproduction studies are not always predictive of the human response, this drug should be used during pregnancy only if clearly needed. Because current information strongly suggests that abnormal blood glucose levels during pregnancy are associated with a higher incidence of congenital anomalies as well as increased neonatal morbidity and mortality, most experts recommend that insulin be used during pregnancy to maintain blood glucose levels as close to normal as possible.

Nursing Mothers:

A small amount of radioactivity has been found in the milk of lactating rats after administration of radiolabeled acarbose. It is not known whether this drug is excreted in human milk. Because many drugs are excreted in human milk, PRECOSE should not be administered to a nursing woman.

Pediatric Use:

Safety and effectiveness of PRECOSE in pediatric patients have not been established.

Geriatric Use:

Of the total number of subjects in clinical studies of PRECOSE in the United States, 27% were 65 and over, while 4% were 75 and over. No overall differences in safety and effectiveness were observed between these subjects and younger subjects. The mean steady-state area under the curve (AUC) and maximum concentrations of acarbose were approximately 1.5 times higher in elderly compared to young volunteers; however, these differences were not statistically significant.

ADVERSE REACTIONS

Digestive Tract

Gastrointestinal symptoms are the most common reactions to PRECOSE. In U.S. placebo-controlled trials, the incidences of abdominal pain, diarrhea, and flatulence were 19%, 31%, and 74% respectively in 1255 patients treated with PRECOSE 50–300 mg t.i.d., whereas the corresponding incidences were 9%, 12%, and 29% in 999 placebo-treated patients.

In a one-year safety study, during which patients kept diaries of gastrointestinal symptoms, abdominal pain and diarrhea tended to return to pretreatment levels over time, and the frequency and intensity of flatulence tended to abate with time. The increased gastrointestinal tract symptoms in patients treated with PRECOSE are a manifestation of the mechanism of action of PRECOSE and are related to the presence of undigested carbohydrate in the lower GI tract.

If the prescribed diet is not observed, the intestinal side effects may be intensified. If strongly distressing symptoms develop in spite of adherence to the diabetic diet prescribed, the doctor must be consulted and the dose temporarily or permanently reduced

Elevated Serum Transaminase Levels

See PRECAUTIONS.

Other Abnormal Laboratory Findings

Small reductions in hematocrit occurred more often in PRECOSE-treated patients than in placebo-treated patients but were not associated with reductions in hemoglobin. Low serum calcium and low plasma vitamin B6 levels were associated with PRECOSE therapy but are thought to be either spurious or of no clinical significance.

Postmarketing Adverse Event Reports

Additional adverse events reported from worldwide postmarketing experience include fulminant hepatitis with fatal outcome, hypersensitive skin reactions (for example rash, erythema, exanthema and uticaria), edema, ileus/subileus, jaundice and/or hepatitis and associated liver damage, thrombocytopenia, and pneumatosis cystoides intestinalis (see PRECAUTIONS).

Pneumatosis Cystoides Intestinalis

There have been rare postmarketing reports of pneumatosis cystoides intestinalis associated with the use of alpha-glucosidase inhibitors, including Precose. Pneumatosis cystoides intestinalis may present with symptoms of diarrhea, mucus discharge, rectal bleeding, and constipation. Complications may include pneumoperitoneum, volvulus, intestinal obstruction, intussusception, intestinal hemorrhage, and intestinal perforation. If pneumatosis cystoides intestinalis is suspected, discontinue Precose and perform the appropriate diagnostic imaging.

OVERDOSAGE

Unlike sulfonylureas or insulin, an overdose of PRECOSE will not result in hypoglycemia. An overdose may result in transient increases in flatulence, diarrhea, and abdominal discomfort which shortly subside. In cases of overdosage the patient should not be given drinks or meals containing carbohydrates (polysaccharides, oligosaccharides and disaccharides) for the next 4–6 hours.

DOSAGE AND ADMINISTRATION

There is no fixed dosage regimen for the management of diabetes mellitus with PRECOSE or any other pharmacologic agent. Dosage of PRECOSE must be individualized on the basis of both effectiveness and tolerance while not exceeding the maximum recommended dose of 100 mg t.i.d. PRECOSE should be taken three times daily at the start (with the first bite) of each main meal. PRECOSE should be started at a low dose, with gradual dose escalation as described below, both to reduce gastrointestinal side effects and to permit identification of the minimum dose required for adequate glycemic control of the patient. If the prescribed diet is not observed, the intestinal side effects may be intensified. If strongly distressing symptoms develop in spite of adherence to the diabetic diet prescribed, the doctor must be consulted and the dose temporarily or permanently reduced.

During treatment initiation and dose titration (see below), one-hour postprandial plasma glucose may be used to determine the therapeutic response to PRECOSE and identify the minimum effective dose for the patient. Thereafter, glycosylated hemoglobin should be measured at intervals of approximately three months. The therapeutic goal should be to decrease both postprandial plasma glucose and glycosylated hemoglobin levels to normal or near normal by using the lowest effective dose of PRECOSE, either as monotherapy or in combination with sulfonylureas, insulin or metformin.

Initial Dosage

The recommended starting dosage of PRECOSE is 25 mg given orally three times daily at the start (with the first bite) of each main meal. However, some patients may benefit from more gradual dose titration to minimize gastrointestinal side effects. This may be achieved by initiating treatment at 25 mg once per day and subsequently increasing the frequency of administration to achieve 25 mg t.i.d.

Maintenance Dosage

Once a 25 mg t.i.d. dosage regimen is reached, dosage of PRECOSE should be adjusted at 4–8 week intervals based on one-hour postprandial glucose or glycosylated hemoglobin levels, and on tolerance. The dosage can be increased from 25 mg t.i.d. to 50 mg t.i.d. Some patients may benefit from further increasing the dosage to 100 mg t.i.d. The maintenance dose ranges from 50 mg t.i.d. to 100 mg t.i.d. However, since patients with low body weight may be at increased risk for elevated serum transaminases, only patients with body weight > 60 kg should be considered for dose titration above 50 mg t.i.d. (see PRECAUTIONS). If no further reduction in postprandial glucose or glycosylated hemoglobin levels is observed with titration to 100 mg t.i.d., consideration should be given to lowering the dose. Once an effective and tolerated dosage is established, it should be maintained.

Maximum Dosage:

The maximum recommended dose for patients ≤ 60 kg is 50 mg t.i.d. The maximum recommended dose for patients > 60 kg is 100 mg t.i.d.

Patients Receiving Sulfonylureas or Insulin:

Sulfonylurea agents or insulin may cause hypoglycemia. PRECOSE given in combination with a sulfonylurea or insulin will cause a further lowering of blood glucose and may increase the potential for hypoglycemia. If hypoglycemia occurs, appropriate adjustments in the dosage of these agents should be made.

HOW SUPPLIED

Repackaged by Aphena Pharma Solutions - TN.
See Repackaging Information for available configurations.

PRECOSE is available as 25 mg, 50 mg or 100 mg round, unscored tablets. Each tablet strength is white to yellow-tinged in color. The 25 mg tablet is coded with the word “PRECOSE” on one side and “25” on the other side. The 50 mg tablet is coded with the word “PRECOSE” and “50” on the same side. The 100 mg tablet is coded with the word “PRECOSE” and “100” on the same side. PRECOSE is available in bottles of 100 and 50 mg strength in unit dose packages of 100.

 | Strength | NDC | Tablet Identification
Bottles of 100: | 25 mg | 50419-863-51 | PRECOSE 25
Bottles of 100: | 50 mg | 50419-861-51 | PRECOSE 50
Bottles of 100: | 100 mg | 50419-862-51 | PRECOSE 100
Unit Dose Packages of 100: | 50 mg | 50419-861-48 | PRECOSE 50

Do not store above 25°C (77°F). Protect from moisture. For bottles, keep container tightly closed.

Bayer HealthCare Pharmaceuticals Inc.
Wayne, NJ 07470
Made in Germany

08753825, R.7 02/12

©2012 Bayer HealthCare Pharmaceuticals Inc.

Repackaging Information

Please reference the How Supplied section listed above for a description of individual tablets or capsules. This drug product has been received by Aphena Pharma - TN in a manufacturer or distributor packaged configuration and repackaged in full compliance with all applicable cGMP regulations. The package configurations available from Aphena are listed below:

Count | 50mg
9000 | 43353-908-09

Store between 20°-25°C (68°-77°F). See USP Controlled Room Temperature. Dispense in a tight light-resistant container as defined by USP. Keep this and all drugs out of the reach of children.

Repackaged by:
Cookeville, TN 38506
20140529SC

PRINCIPAL DISPLAY PANEL - 50mg

NDC 43353-908 - Acarbose (Precose®) 50mg - Rx Only